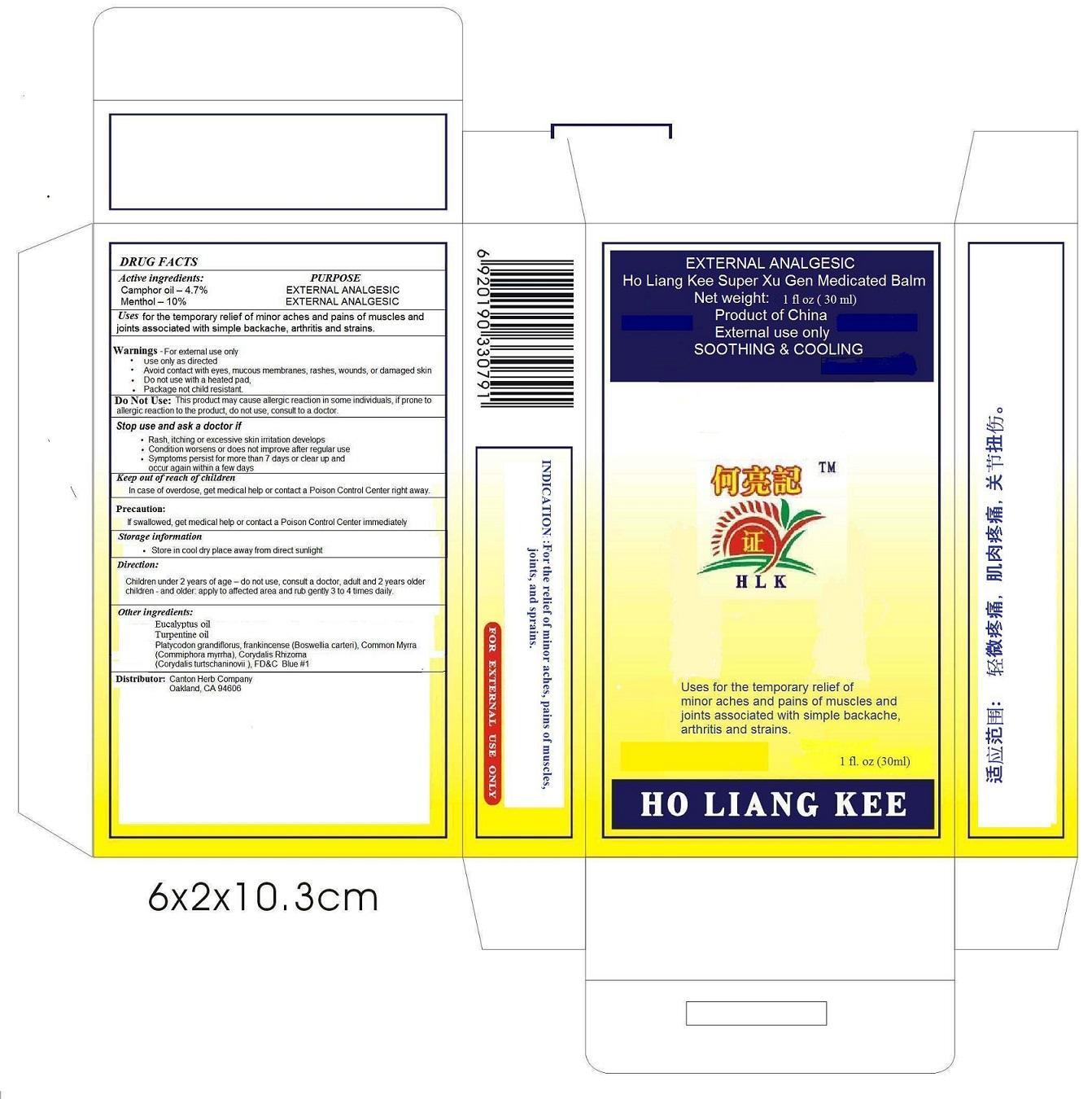 DRUG LABEL: Ho Liang Kee
NDC: 62266-3245 | Form: OIL
Manufacturer: Changshu Starsea Pharmaceutical Co., Ltd.
Category: otc | Type: HUMAN OTC DRUG LABEL
Date: 20140222

ACTIVE INGREDIENTS: CAMPHOR OIL 4.7 g/100 g; MENTHOL 10 g/100 g
INACTIVE INGREDIENTS: EUCALYPTUS OIL; TURPENTINE OIL; PLATYCODON GRANDIFLORUS ROOT; FRANKINCENSE; MYRRH; CORYDALIS YANHUSUO TUBER; FD&C BLUE NO. 1

Ho Liang Kee

Active ingredients

Camphor Oil 4.7%

Menthol 10%

Purpose

EXTERNAL ANALGESIC

Keep out of reach of Children

In case of over dose, get medical help or contact a poison control center right away.

INDICATIONS AND USAGE

Uses for the temporary relief of minor aches and pains of muscles and joints associated with simple backache, arthritis & strains

Warnings - For external use only

- Use only as directed
- Avoid contact with eyes, mucous membranes, rashes, wounds or damaged skin.
- Do not use with a heated pad
- Package not Child resistant

Do Not Use: This product may cause allergic reactions in some individuals, if prone to allergic reaction to the product, do not use, consult to a doctor.

Stop use and ask a doctor

- Rash, itching or excessive skin irritation develops
- Condition worsens or does not improve after regular use
- Symptoms persist for more than 7 days or clear up and occur again within a few days

Precaution:

If swallowed, get medical help or contact a Poison Control Center immediately

Stoarage information

- Store in cool dry place away from direct sunlight.

Direction

Children under 2 years of age: do not use, consult a doctor, adult and 2 years older children- and older : apply to affected area and rub gently 3 to 4 times daily.

Other ingredients

Eucalyptus oil

Turpentine oil

Platycodon grandiflorus

Frankincense (Boswelli carteri)

Common myrra (Commiphora myrra)

Corydalis Rhizoma (Cordalis turtschaninovii)

FD&C Blue No. 1

Distributor:

Canton Herb company
Oakland, CA 94606